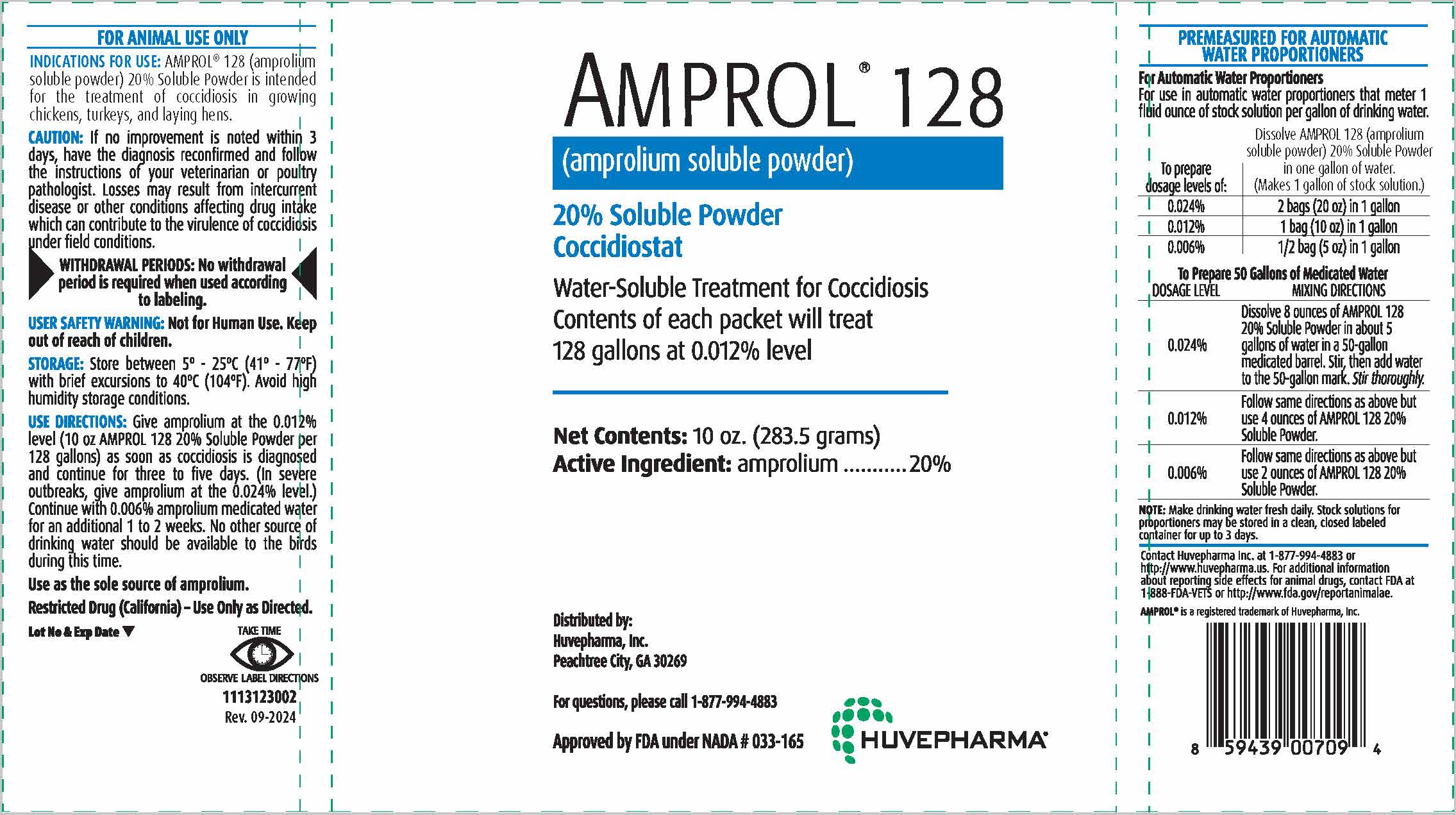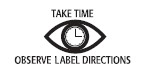 DRUG LABEL: Amprol
NDC: 23243-9709 | Form: POWDER
Manufacturer: Huvepharma, Inc.
Category: animal | Type: OTC ANIMAL DRUG LABEL
Date: 20241031

ACTIVE INGREDIENTS: AMPROLIUM 0.2 g/1 g

AMPROL® 128

(amprolium soluble powder)

20% Soluble Powder
Coccidiostat

Water-Soluble Treatment for Coccidiosis
Contents of each packet will treat
128 gallons at 0.012% level

ACTIVE INGREDIENT

Net Contents: 10 oz. (283.5 grams)
Active Ingredient: amprolium...........20%

Distributed by:
Huvepharma, Inc.
Peachtree City, GA 30269

For questions, please call 1-877-994-4883

Approved by FDA under NADA # 033-165

VETERINARY INDICATIONS

FOR ANIMAL USE ONLY

INDICATIONS FOR USE: AMPROL® 128 (amprolium soluble powder)
20% Soluble Powder is intended for the treatment of coccidiosis in growing
chickens, turkeys, and laying hens.

PRECAUTIONS

CAUTION: If no improvement is noted within 3 days, have the diagnosis reconfirmed and follow
the instructions of your veterinarian or poultry pathologist. Losses may result from intercurrent
disease or other conditions affecting drug intake which can contribute to the virulence of coccidiosis
under field conditions.

RESIDUE WARNING

WITHDRAWAL PERIODS: No withdrawal period is required when used according
to labeling.

USER SAFETY WARNINGS

USER SAFETY WARNING: Not for Human Use. Keep out of reach of children.

STORAGE AND HANDLING

STORAGE: Store between 5º - 25ºC (41º - 77ºF) with brief excursions to 40ºC (104ºF). Avoid high
humidity storage conditions.

INDICATIONS AND USAGE

USE DIRECTIONS: Give amprolium at the 0.012% level (10 oz AMPROL 128 20% Soluble Powder per
128 gallons) as soon as coccidiosis is diagnosed and continue for three to five days. (In severe
outbreaks, give amprolium at the 0.024% level.) Continue with 0.006% amprolium medicated water
for an additional 1 to 2 weeks. No other source of drinking water should be available to the birds
during this time.

Use as the sole source of amprolium.

Restricted Drug (California) – Use Only as Directed.

Lot No & Exp Date

DOSAGE AND ADMINISTRATION

PREMEASURED FOR AUTOMATIC WATER PROPORTIONERS

For Automatic Water Proportioners
For use in automatic water proportioners that meter 1
fluid ounce of stock solution per gallon of drinking water.

To prepare dosage levels of: | Dissolve AMPROL 128; (amprolium soluble powder) 20% Soluble Powder; in one gallon of water.; (Makes 1 gallon of stock solution.)
0.024% | 2 bags (20 oz) in 1 gallon
0.012% | 1 bag (10 oz) in 1 gallon
0.006% | ½ bag (5 oz) in 1 gallon

To Prepare 50 Gallons of Medicated Water

DOSAGE LEVEL | MIXING DIRECTIONS
0.024% | Dissolve 8 ounces of AMPROL 128 20% Soluble Powder in about 5 gallons of water in a 50-gallon; medicated barrel. Stir, then add water to the 50-gallon mark. Stir thoroughly.
0.012% | Follow same directions as above but use 4 ounces of AMPROL 128 20% Soluble Powder.
0.006% | Follow same directions as above but use 2 ounces of AMPROL 128 20% Soluble Powder.

NOTE: Make drinking water fresh daily. Stock solutions for proportioners may be stored in a clean,
closed labeled container for up to 3 days.

ADVERSE REACTIONS

Contact Huvepharma Inc. at 1-877-994-4883 or http:/www.huvepharma.us.
For additional information about reporting side effects for animal
drugs, contact FDA at 1-888-FDA-VETS or http://www.fda.gov/reportanimalae.

AMPROL® is a registered trademark of Huvepharma, Inc.